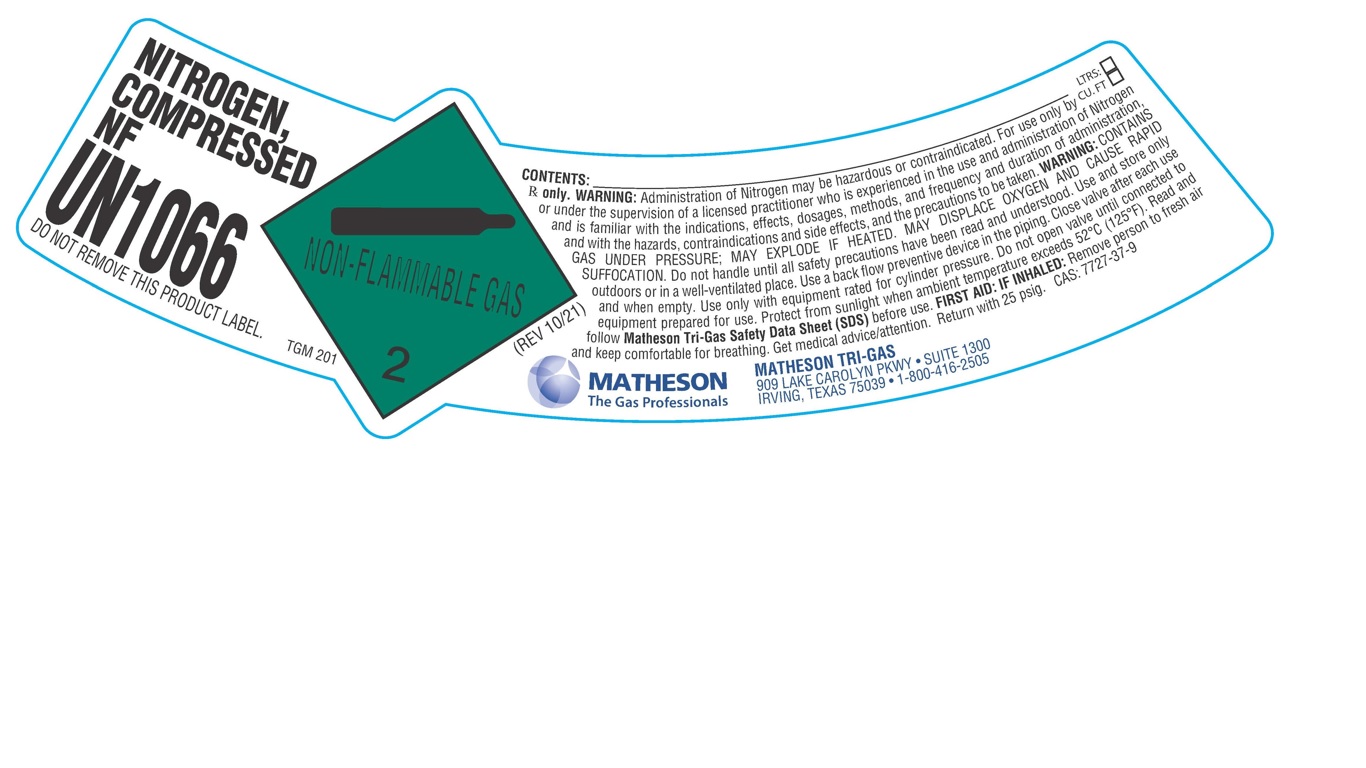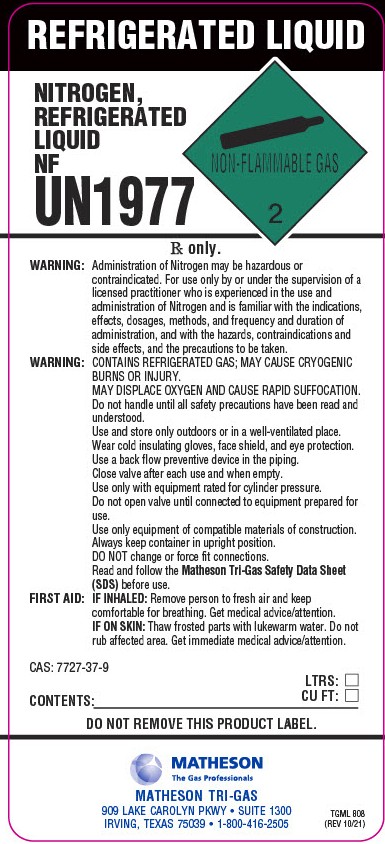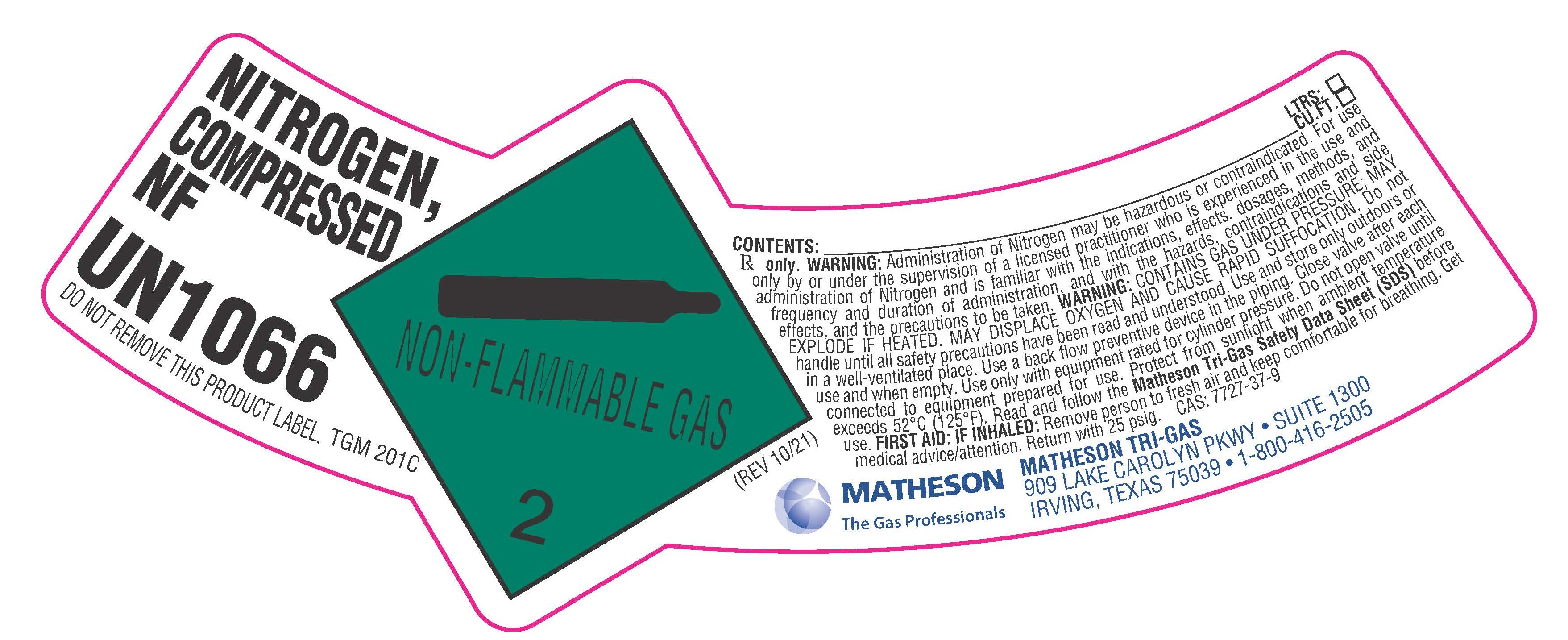 DRUG LABEL: Nitrogen
NDC: 55037-211 | Form: GAS
Manufacturer: Matheson Tri-Gas, Inc.
Category: animal | Type: PRESCRIPTION ANIMAL DRUG LABEL
Date: 20260121

ACTIVE INGREDIENTS: NITROGEN 992 mL/1 L

Nitrogen

PACKAGE LABEL

NITROGEN, COMPRESSED NF

UN1066

DO NOT REMOVE THIS PRODUCT LABEL.

CONTENTS: LTRS: CU.FT.

Rx only. WARNING: Administration of Nitrogen may be hazardous or contraindicated. For use only by or under the supervision of a licensed practitioner who is experienced in the use and administration of Nitrogen and is familiar with the indications, effects, dosages, methods, and frequency and duration of administration, and with the hazards, contraindications and side effects, and the precautions to be taken. WARNING: CONTAINS GAS UNDER PRESSURE; MAY EXPLODE IF HEATED. MAY DISPLACE OXYGEN AND CAUSE RAPID SUFFOCATION. Do not handle until all safety precautions have been read and understood. Use and store only outdoors or in a well-ventilated place. Use a back flow preventive device in the piping. Close valve after each use and when empty. Use only with equipment rated for cylinder pressure. Do not open valve until connected to equipment prepared for use. Protect from sunlight when ambient temperature exceeds 52 C (125 F). Read and follow Matheson Tri-Gas Safety Data Sheet (SDS) before use. FIRST AID: IF INHALED: Remove person to fresh air and keep comfortable for breathing. Get medical advice/attention. Return with 25 psig. CAS: 7727-37-9

MATHESON The Gas Professionals

MATHESON TRI-GAS

909 LAKE CAROLYN PKWY. SUITE 1300

IRVING, TEXAS 75039 . 1-800-416-2505

PACKAGE LABEL

NITROGEN, COMPRESSED NF

UN1066

DO NOT REMOVE THIS PRODUCT LABEL.

CONTENTS: LTRS: CU.FT.

Rx only. WARNING: Administration of Nitrogen may be hazardous or contraindicated. For use only by or under the supervision of a licensed practitioner who is experienced in the use and administration of Nitrogen and is familiar with the indications, effects, dosages, methods, and frequency and duration of administration, and with the hazards, contraindications and side effects, and the precautions to be taken. WARNING: CONTAINS GAS UNDER PRESSURE; MAY EXPLODE IF HEATED. MAY DISPLACE OXYGEN AND CAUSE RAPID SUFFOCATION. Do not handle until all safety precautions have been read and understood. Use and store only outdoors or in a well-ventilated place. Use a back flow preventive device in the piping. Close valve after each use and when empty. Use only with equipment rated for cylinder pressure. Do not open valve until connected to equipment prepared for use. Protect from sunlight when ambient temperature exceeds 52 C (125 F). Read and follow the Matheson Tri-Gas Safety Data Sheet (SDS) before use. FIRST AID: IF INHALED: Remove person to fresh air and keep comfortable for breathing. Get medical advice/attention. Return with 25 psig. CAS: 7727-37-9

MATHESON The Gas Professionals

MATHESON TRI-GAS

909 LAKE CAROLYN PKWY. SUITE 1300

IRVING, TEXAS 75039 . 1-800-416-2505

PACKAGE LABEL

REFRIGERATED LIQUID

NITROGEN, REFRIGERATED LIQUID NF

UN1977

Rx only.

WARNING: Administration of Nitrogen may be hazardous or contraindicated. For use only by or under the supervision of a licensed practitioner who is experienced in the use and administration of Nitrogen and is familiar with the indications, effects, dosages, methods, and frequency and duration of administration, and with the hazards, contraindications and side effects, and the precautions to be taken.

WARNING: CONTAINS REFRIGERATED GAS; MAY CAUSE CRYOGENIC BURNS OR INJURY. MAY DISPLACE OXYGEN AND CAUSE RAPID SUFFOCATION.

Do not handle until all safety precautions have been read and understood. Use and store only outdoors or in a well-ventilated place. Wear cold insulating gloves, face shield, and eye protection. Use a back flow preventive device in the piping. Close valve after each use and when empty. Use only with equipment rated for cylinder pressure. Do not open valve until connected to equipment prepared for use. Use only with equipment of compatible materials of construction. Always keep container in upright position. DO NOT change or force fit connections. Read and follow the Matheson Tri-Gas Safety Data Sheet (SDS) before use.

FIRST AID: IF INHALED: Remove person to fresh air and keep comfortable for breathing. Get medical advice/attention.

IF ON SKIN: Thaw frosted parts with lukewarm water. Do not rub affected area. Get immediate medical advice/attention.

CAS: 7727-37-9

CONTENTS: LTRS: CU FT:

DO NOT REMOVE THIS PRODUCT LABEL.

MATHESON The Gas Professionals

MATHESON TRI-GAS

909 LAKE CAROLYN PKWY. SUITE 1300

IRVING, TEXAS 75039 . 1-800-416-2505